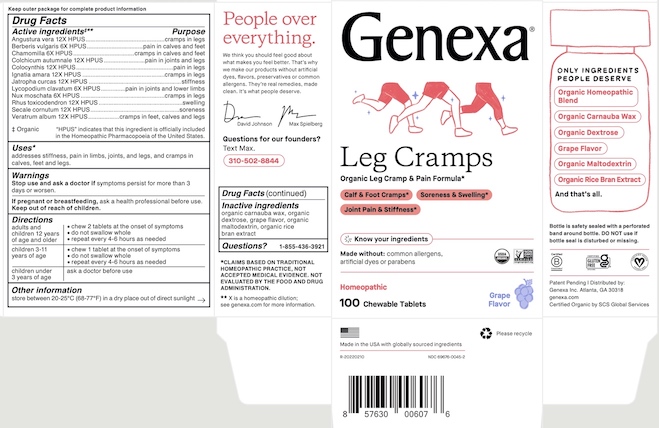 DRUG LABEL: Genexa Leg Cramps
NDC: 69676-0045 | Form: TABLET, CHEWABLE
Manufacturer: Genexa Inc.
Category: homeopathic | Type: HUMAN OTC DRUG LABEL
Date: 20220724

ACTIVE INGREDIENTS: MATRICARIA CHAMOMILLA 6 [hp_X]/1 1; ANGOSTURA BARK 12 [hp_X]/1 1; BERBERIS VULGARIS ROOT BARK 6 [hp_X]/1 1; CITRULLUS COLOCYNTHIS FRUIT PULP 12 [hp_X]/1 1; STRYCHNOS IGNATII SEED 12 [hp_X]/1 1; JATROPHA CURCAS SEED 12 [hp_X]/1 1; LYCOPODIUM CLAVATUM SPORE 6 [hp_X]/1 1; NUTMEG 6 [hp_X]/1 1; TOXICODENDRON PUBESCENS LEAF 12 [hp_X]/1 1; CLAVICEPS PURPUREA SCLEROTIUM 12 [hp_X]/1 1; VERATRUM ALBUM ROOT 12 [hp_X]/1 1; COLCHICUM AUTUMNALE BULB 12 [hp_X]/1 1
INACTIVE INGREDIENTS: CARNAUBA WAX; MALTODEXTRIN; RICE BRAN; DEXTROSE

LEG CRAMPS

Keep outer package for complete product information

Drug Facts

Active ingredients‡**

Angustura vera 12X HPUS

Berberis vulgaris 6X HPUS

Chamomilla 6X HPUS

Colchicum autumnale 12X HPUS

Colocynthis 12X HPUS

Ignatia amara 12X HPUS

Jatropha curcas 12X HPUS

Lycopodium clavatum 6X HPUS

Nux moschata 6X HPUS

Rhus toxicodendron 12X HPUS

Secale cornutum 12X HPUS

Veratrum album 12X HPUS

‡ Organic

"HPUS" indicates that this ingredient is officially included in the Homeopathic Pharmacopoeia of the United States.

Purposes

cramps in legs

pain in calves and feet

cramps in calves and feet

pain in joints and legs

pain in legs

cramps in legs

stiffness

pain in joints and lower limbs

cramps in legs

swelling

soreness

cramps in feet, calves and legs

Uses*

addresses stiffness, pain in limbs, joints, and legs, and cramps in calves, feet and legs.

Warnings

Stop use and ask a doctor if symptoms persist for more than 3 days or worsen.

PREGNANCY OR BREAST FEEDING

If pregnant or breastfeeding, ask a health professional before use.

Keep out of reach of children.

Directions

adults and children 12 years of age and older | - chew 2 tablets at the onset of symptoms - do not swallow whole - repeat every 4-6 hours as needed
children 3-11 years of age | - chew 1 tablet at the onset of symptoms - do not swallow whole - repeat every 4-6 hours as needed
children under 3 years of age | ask a doctor before use

Other information

store between 20-25°C (68-77°F) in a dry place out of direct sunlight

Inactive ingredients

organic carnauba wax, organic dextrose, grape flavor, organic maltodextrin, organic rice bran extract

Questions?

1-855-436-3921

*CLAIMS BASED ON TRADITIONAL HOMEOPATHIC PRACTICE, NOT ACCEPTED MEDICAL EVIDENCE. NOT EVALUATED BY THE FOOD AND DRUG ADMINISTRATION.
** X is a homeopathic dilution; see genexa.com for more information.

Bottle is safety sealed with a perforated band around bottle. DO NOT use if bottle seal is disturbed or missing.
Patent Pending | Distributed by:
Genexa Inc. Atlanta, GA 30318
genexa.com
Certified Organic by SCS Global Services

Made in the USA with globally sourced ingredients

R-20220210

NDC 69676-0045-2

PACKAGE LABEL

Genexa®
Leg Cramps
Organic Leg Cramp & Pain Formula*

Calf & Foot Cramps*
Soreness & Swelling*
Joint Pain & Stiffness*
Know your ingredients

Made without: common allergens, artificial dyes, or parabens

Homeopathic

100 Chewable Tablets

Grape Flavor